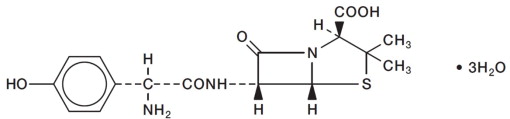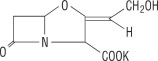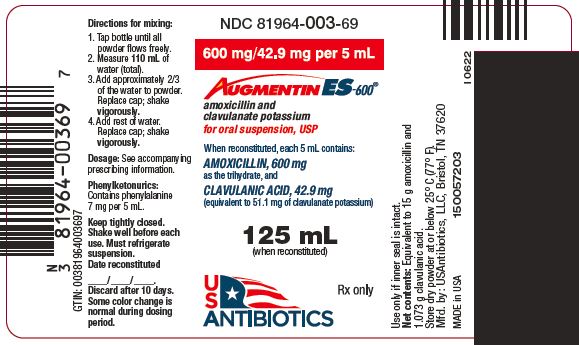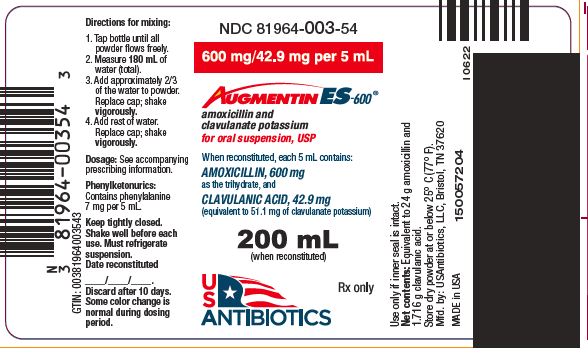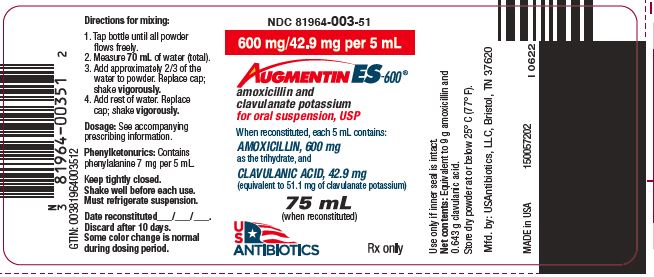 DRUG LABEL: AUGMENTIN ES-600

NDC: 81964-003 | Form: FOR SUSPENSION
Manufacturer: USAntibiotics, LLC

Category: prescription | Type: HUMAN PRESCRIPTION DRUG LABEL
Date: 20241224

ACTIVE INGREDIENTS: AMOXICILLIN
 600 mg/5 mL; CLAVULANATE POTASSIUM
 42.9 mg/5 mL
INACTIVE INGREDIENTS: SILICON DIOXIDE; XANTHAN GUM; ASPARTAME; CARBOXYMETHYLCELLULOSE SODIUM

HIGHLIGHTS OF PRESCRIBING INFORMATION

These highlights do not include all the information needed to use AUGMENTIN ES-600®, safely and effectively. See full prescribing information for AUGMENTIN ES-600®.
AUGMENTIN ES-600® (amoxicillin and clavulanate potassium) for oral suspension
Initial U.S. Approval: 2001

RECENT MAJOR CHANGES

Indications and Usage (1)

Dosage and Administration, Dosage in Pediatric Patients (2.2)

Warnings and Precautions

Drug-Induced Enterocolitis Syndrome (DIES) (5.3)

12/2024

12/2024

5/2024

1 INDICATIONS AND USAGE

AUGMENTIN ES-600 is a combination of amoxicillin, a penicillin-class antibacterial and clavulanate potassium, a beta-lactamase inhibitor, indicated for the treatment of pediatric patients aged 3 months to 12 years weighing less than or equal to 40 kg with:

- Recurrent or persistent acute otitis media due to S. pneumoniae (penicillin MICs less than or equal to 2 mcg/mL), H. influenzae (including beta-lactamase-producing strains), or M. catarrhalis (including beta-lactamase-producing strains) characterized by the following risk factors (1): Antibacterial exposure for acute otitis media within the preceding 3 months, and either of the following: 1) age 2 years, or younger or 2) day care attendance.

Limitations of Use

AUGMENTIN ES-600 is not indicated for the treatment of acute otitis media due to S. pneumoniae with penicillin MIC greater than or equal to 4 mcg/mL. Acute otitis media due to S. pneumoniae alone can be treated with amoxicillin. Therapy may be instituted prior to obtaining the results from bacteriological studies when there is reason to believe the infection may involve both S. pneumoniae (penicillin MIC less than or equal to 2 mcg/mL) and the beta lactamase producing organisms listed above. (1)

Usage

To reduce the development of drug-resistant bacteria and maintain the effectiveness of AUGMENTIN ES-600 and other antibacterial drugs, AUGMENTIN ES-600 should be used only to treat or prevent infections that are proven or strongly suspected to be caused by bacteria. (1)

2 DOSAGE AND ADMINISTRATION

- Pediatric Patients aged 3 months to 12 years weighing less than or equal to 40 kg: 90 mg/kg/day divided every 12 hours, administered for 10 days. (2)

3 DOSAGE FORMS AND STRENGTHS

For oral suspension: 600 mg/42.9 mg per 5 mL.

4 CONTRAINDICATIONS

- History of a serious hypersensitivity reaction (e.g., anaphylaxis or Stevens-Johnson syndrome) to AUGMENTIN ES-600 or any other beta-lactams (e.g., penicillins or cephalosporins). (4.1)
- History of cholestatic jaundice/hepatic dysfunction associated with AUGMENTIN ES-600. (4.2)

5 WARNINGS AND PRECAUTIONS

- Serious (including fatal) hypersensitivity reactions: Discontinue AUGMENTIN ES-600 if a reaction occurs and institute appropriate therapy. (5.1)
- Severe cutaneous adverse reactions (SCAR): Monitor closely. Discontinue if rash progresses. (5.2)
- Drug-induced enterocolitis syndrome (DIES) has been reported with use of amoxicillin, a component of AUGMENTIN ES-600. If this occurs, discontinue AUGMENTIN ES-600 and institute appropriate therapy. (5.3)
- Hepatic dysfunction and cholestatic jaundice: Discontinue if signs/symptoms of hepatitis occur. Monitor liver function tests in patients with hepatic impairment. (5.4)
- Clostridioides difficile-associated diarrhea (CDAD) (ranging from mild diarrhea to fatal colitis): Evaluate patients if diarrhea occurs. (5.5)
- Patients with mononucleosis who receive AUGMENTIN ES-600 develop skin rash. Avoid AUGMENTIN ES-600 use in these patients. (5.6)

6 ADVERSE REACTIONS

The most frequently reported adverse reactions (incidence rate > 4 %) were coughing, vomiting, contact dermatitis (i.e., diaper rash), fever, upper respiratory tract infection, and diarrhea. (6.1)

To report SUSPECTED ADVERSE REACTIONS, contact USAntibiotics, LLC at 1-844-454-5532 or FDA at 1-800-FDA-1088 or www.fda.gov/medwatch.

7 DRUG INTERACTIONS

- Co-administration with probenecid is not recommended. (7.1)
- Concomitant use of AUGMENTIN ES-600 with oral anticoagulants may increase the prolongation of prothrombin time. (7.2)
- Co-administration with allopurinol increases the risk of rash. (7.3)
- AUGMENTIN ES-600 may reduce efficacy of oral contraceptives. (7.4)

FULL PRESCRIBING INFORMATION

1 INDICATIONS AND USAGE

AUGMENTIN ES-600 is indicated for the treatment of pediatric patients aged 3 months to 12 years weighing less than or equal to 40 kg with:

- Recurrent or persistent acute otitis media due to S. pneumoniae (penicillin MICs less than or equal to 2 mcg/mL), H. influenzae (including beta-lactamase-producing strains), or M. catarrhalis (including beta-lactamase-producing strains) characterized by the following risk factors:
  - Antibacterial drug exposure for acute otitis media within the preceding 3 months, and either of the following: 1) age 2 years, or younger or 2) day care attendance [see Microbiology (12.4)].

Limitations of Use

AUGMENTIN ES-600 is not indicated for the treatment of acute otitis media due to S. pneumoniae with penicillin MIC greater than or equal to 4 mcg/mL. Acute otitis media due to S. pneumoniae alone can be treated with amoxicillin. Therapy may be instituted prior to obtaining the results from bacteriological studies when there is reason to believe the infection may involve both S. pneumoniae (penicillin MIC less than or equal to 2 mcg/mL) and the beta-lactamase-producing organisms listed above.

Usage

To reduce the development of drug-resistant bacteria and maintain the effectiveness of AUGMENTIN ES-600 and other antibacterial drugs, AUGMENTIN ES-600 should be used only to treat or prevent infections that are proven or strongly suspected to be caused by susceptible bacteria. When culture and susceptibility information are available, they should be considered in selecting or modifying antibacterial therapy. In the absence of such data, local epidemiology and susceptibility patterns may contribute to the empiric selection of therapy.

2 DOSAGE AND ADMINISTRATION

2.1 Important Administration Instructions

To minimize the potential for gastrointestinal intolerance, AUGMENTIN ES-600 should be taken at the start of a meal. Absorption of clavulanate potassium may be enhanced when AUGMENTIN ES-600 is administered at the start of a meal.

2.2 Dosage in Pediatric Patients

Pediatric patients aged 3 months to 12 years weighing less than or equal to 40 kg: Based on the amoxicillin component (600 mg/5 mL), the recommended dose of AUGMENTIN ES-600 is 90 mg/kg/day divided every 12 hours, administered for 10 days (see Table 1 as a general example guideline for attainment of this dosage). This dose provides 6.4 mg/kg/day of the clavulanic acid component.

Table 1: General Dosage Guidelines for AUGMENTIN ES-600 in Pediatric Patients

Body Weight (kg) | Volume of AUGMENTIN ES-600 for oral suspensionproviding 90 mg/kg/day
8 | 3 mL twice daily
12 | 4.5 mL twice daily
16 | 6 mL twice daily
20 | 7.5 mL twice daily
24 | 9 mL twice daily
28 | 10.5 mL twice daily
32 | 12 mL twice daily
36 | 13.5 mL twice daily
40 | 15 mL twice daily

Pediatric patients weighing greater than 40 kg: Experience with AUGMENTIN ES-600 in this group is not available.

2.3 Dosage in Adult Patients

Experience with AUGMENTIN ES-600 in adults is not available and adults who have difficulty swallowing should not be given AUGMENTIN ES-600 in place of the 500 mg or 875 mg tablet of AUGMENTIN.

2.4 Dosage in Patients with Hepatic Impairment

Hepatically impaired patients should be dosed with caution and hepatic function monitored at regular intervals [see Warnings and Precautions (5.4)].

2.5 Preparation of the Oral Suspension

Prepare the suspension at time of dispensing as follows: Tap bottle until all powder flows freely. Measure the total amount of water (see Table 2) to be added in two parts. Add approximately 2/3 of the total amount of water for reconstitution, replace cap and shake vigorously to suspend powder. Add remainder of the water (that had been measured), replace cap and again shake vigorously.

Table 2: Volume of Water for Reconstituting AUGMENTIN ES-600

Bottle Size | Amount of Water Required for Reconstitution
75 mL | 70 mL
125 mL | 110 mL
200 mL | 180 mL

Each 5 mL will contain 600 mg of amoxicillin as the trihydrate, and 42.9 mg of clavulanic acid as the potassium salt.

Shake oral suspension well before each use. Suspension must be refrigerated. Discard after 10 days. Suspension is off-white at time of reconstitution; some color change is normal during the dosing period.

Flavoring Information: For patients who wish to alter the taste of AUGMENTIN ES-600, immediately after reconstitution, 1 drop of FLAVORx® (apple, banana cream, bubble gum, cherry, or watermelon flavor) may be added for every 5 mL of AUGMENTIN ES-600. The resulting suspension is stable for 10 days under refrigeration. Stability of AUGMENTIN ES-600 when mixed with other flavors other than the 5 flavors listed above has not been evaluated.

2.6 Switching between Dosage Forms and between Strengths

AUGMENTIN ES-600 does not contain the same amount of clavulanic acid (as the potassium salt) as any of the other suspensions of AUGMENTIN. AUGMENTIN ES-600 contains 42.9 mg of clavulanic acid per 5 mL, whereas the 200 mg/28.5 mg per 5 mL suspension of AUGMENTIN contains 28.5 mg clavulanic acid per 5 mL and the 400 mg/57 mg per 5 mL suspension of AUGMENTIN contains 57 mg clavulanic acid per 5 mL. Therefore, the 200 mg/28.5 mg per 5 mL and 400 mg/57 mg per 5 mL suspensions of AUGMENTIN should not be substituted for AUGMENTIN ES-600 as they are not interchangeable.

3 DOSAGE FORMS AND STRENGTHS

Augmentin ES 600 for Oral Suspension: 600 mg/42.9 mg per 5 mL: Strawberry cream-flavored for oral suspension (each 5 mL of reconstituted suspension contains 600 mg of amoxicillin as the trihydrate, and 42.9 mg of clavulanic acid as the potassium salt).

4 CONTRAINDICATIONS

4.1 Serious Hypersensitivity Reactions

AUGMENTIN ES-600 is contraindicated in patients with a history of serious hypersensitivity reactions (e.g., anaphylaxis or Stevens-Johnson syndrome) to amoxicillin, clavulanate, or to other beta-lactam antibacterial drugs (e.g., penicillins and cephalosporins).

4.2 Cholestatic Jaundice/Hepatic Dysfunction

AUGMENTIN ES-600 is contraindicated in patients with a previous history of cholestatic jaundice/hepatic dysfunction associated with treatment with amoxicillin and clavulanate potassium.

5 WARNINGS AND PRECAUTIONS

5.1 Serious Allergic Reactions, including Anaphylaxis

Serious and occasionally fatal hypersensitivity (anaphylactic) reactions have been reported in patients receiving beta-lactam antibacterials, including AUGMENTIN ES-600. These reactions are more likely to occur in individuals with a history of penicillin hypersensitivity and/or a history of sensitivity to multiple allergens. Before initiating therapy with AUGMENTIN ES-600, careful inquiry should be made concerning previous hypersensitivity reactions to penicillins, cephalosporins, or other allergens. If an allergic reaction occurs, discontinue AUGMENTIN ES-600 and institute appropriate therapy.

5.2 Severe Cutaneous Adverse Reactions

AUGMENTIN ES-600 may cause severe cutaneous adverse reactions (SCAR), such as Stevens-Johnson syndrome (SJS), toxic epidermal necrolysis (TEN), drug reaction with eosinophilia and systemic symptoms (DRESS), and acute generalized exanthematous pustulosis (AGEP). If patients develop a skin rash, they should be monitored closely, and AUGMENTIN ES-600 discontinued if lesions progress.

5.3 Drug-Induced Enterocolitis Syndrome (DIES)

Drug-induced enterocolitis syndrome (DIES) has been reported with use of amoxicillin, a component of AUGMENTIN ES-600 [see Adverse Reactions (6.2)], with most cases occurring in pediatric patients  18 years of age. DIES is a non-IgE mediated hypersensitivity reaction characterized by protracted vomiting occurring 1 to 4 hours after drug ingestion in the absence of skin or respiratory symptoms. DIES may be associated with pallor, lethargy, hypotension, shock, diarrhea within 24 hours after ingesting amoxicillin, and leukocytosis with neutrophilia. If DIES occurs, discontinue AUGMENTIN ES-600 and institute appropriate therapy.

5.4 Hepatic Dysfunction

Use AUGMENTIN ES-600 with caution in patients with evidence of hepatic dysfunction. Hepatic toxicity associated with the use of AUGMENTIN ES-600 is usually reversible. Deaths have been reported (fewer than one death reported per estimated four million prescriptions worldwide). These have generally been cases associated with serious underlying diseases or concomitant medications [see Contraindications (4.2) and Adverse Reactions (6.2)].

5.5 Clostridioides difficile-Associated Diarrhea (CDAD)

Clostridioides difficile-associated diarrhea (CDAD) has been reported with use of nearly all antibacterial agents, including AUGMENTIN ES-600, and may range in severity from mild diarrhea to fatal colitis. Treatment with antibacterial agents alters the normal flora of the colon leading to overgrowth of C. difficile.

C. difficile produces toxins A and B which contribute to the development of CDAD. Hypertoxin-producing strains of C. difficile cause increased morbidity and mortality, as these infections can be refractory to antimicrobial therapy and may require colectomy. CDAD must be considered in all patients who present with diarrhea following antibacterial drug use. Careful medical history is necessary since CDAD has been reported to occur over two months after the administration of antibacterial agents.

If CDAD is suspected or confirmed, ongoing antibacterial drug use not directed against C. difficile may need to be discontinued. Appropriate fluid and electrolyte management, protein supplementation, antibacterial treatment of C. difficile, and surgical evaluation should be instituted as clinically indicated.

5.6 Skin Rash in Patients with Mononucleosis

A high percentage of patients with mononucleosis who receive amoxicillin develop an erythematous skin rash. Avoid AUGMENTIN ES-600 use in patients with mononucleosis.

5.7 Potential for Microbial Overgrowth

The possibility of superinfections with mycotic or bacterial pathogens should be kept in mind during therapy. If superinfections occur (usually involving Pseudomonas spp. or Candida spp.), the drug should be discontinued, and appropriate therapy instituted.

5.8 Phenylketonurics

AUGMENTIN ES-600 contains aspartame which contains phenylalanine. Each 5 mL of suspension of AUGMENTIN ES-600 contains 7 mg phenylalanine.

5.9 Development of Drug-Resistant Bacteria

Prescribing AUGMENTIN ES-600 in the absence of a proven or strongly suspected bacterial infection or a prophylactic indication is unlikely to provide benefit to the patient and increases the risk of the development of drug-resistant bacteria.

6 ADVERSE REACTIONS

The following clinically significant adverse reactions are described elsewhere in labeling:

- Anaphylactic reactions [see Warnings and Precautions (5.1)]
- Severe Cutaneous Adverse Reactions (SCAR) [see Warnings and Precautions (5.2)]
- Drug-Induced Enterocolitis Syndrome (DIES) [see Warnings and Precautions (5.3)]
- Hepatic Dysfunction [see Warnings and Precautions (5.4)]
- Clostridioides difficile-Associated Diarrhea (CDAD) [see Warnings and Precautions (5.5)]
- Skin Rash in Patients with Mononucleosis [see Warnings and Precautions (5.6)]

6.1 Clinical Trial Experience

Because clinical trials are conducted under widely varying conditions, adverse reaction rates observed in the clinical trials of a drug cannot be directly compared to rates in the clinical trials of another drug and may not reflect the rates observed in practice.

Two clinical trials evaluated the safety of a 10-day treatment course of AUGMENTIN ES-600 90/6.4 mg/kg/day, divided every 12 hours, in pediatric patients with acute otitis media [see Clinical Studies (14)]. The first trial involved 521 pediatric patients (3 months to 50 months) and the second trial involved 450 pediatric patients (3 months to 12 years). In the intent-to-treat population of the first trial of 521 patients, the most frequently reported adverse events were vomiting (7%), fever (6%), contact dermatitis (i.e., diaper rash) (6%), upper respiratory tract infection (4%), and diarrhea (4%). Protocol-defined diarrhea (i.e., 3 or more watery stools in one day or 2 watery stools per day for 2 consecutive days as recorded on diary cards) occurred in 13% of patients.

The primary objective of the second study was to compare the safety of AUGMENTIN ES-600 (90/6.4 mg/kg/day, divided every 12 hours) to AUGMENTIN (45/6.4 mg/kg/day, divided every 12 hours) for ten days. There was no statistically significant difference between treatments in the proportion of patients with 1 or more adverse events. The most frequently reported adverse reactions for AUGMENTIN ES-600 and the comparator of AUGMENTIN were coughing (12% versus 7%), vomiting (7% versus 8%), contact dermatitis (i.e., diaper rash, 6% versus 5%), fever (6% versus 4%), and upper respiratory infection (3% versus 9%), respectively. The frequencies of protocol-defined diarrhea with AUGMENTIN ES-600 (11%) and AUGMENTIN (9%) were not statistically different. Two patients in the group treated with AUGMENTIN ES-600 and one patient in the group treated with AUGMENTIN were withdrawn due to diarrhea.

6.2 Postmarketing Experience

The following adverse reactions have been identified during postmarketing use of AUGMENTIN products, including AUGMENTIN ES-600. Because these reactions are reported voluntarily from a population of unknown size, it is not always possible to reliably estimate their frequency or establish a causal relationship to drug exposure.

Gastrointestinal: Drug-induced enterocolitis syndrome (DIES), diarrhe, nausea, vomiting, indigestion, gastritis, stomatitis, glossitis, black “hairy” tongue, mucocutaneous candidiasis, enterocolitis, and hemorrhagic/pseudomembranous colitis. Onset of pseudomembranous colitis symptoms may occur during or after antibacterial treatment [see Warnings and Precautions (5.5)].

Immune: Hypersensitivity reactions, anaphylactic/anaphylactoid reactions (including shock), angioedema, serum sickness-like reactions (urticaria or skin rash accompanied by arthritis, arthralgia, myalgia, and frequently fever), hypersensitivity vasculitis[see Warnings and Precautions (5.1)].

Skin and Appendages: Rashes, pruritus, urticaria, erythema multiforme, SJS, TEN, DRESS, AGEP, exfoliative dermatitis, and linear IgA bullous dermatosis [see Warnings and Precautions (5.1, 5.2, 5.6)].

Liver: A moderate rise in AST (SGOT) and/or ALT (SGPT) has been noted in patients treated with ampicillin-class antibacterials. Hepatic dysfunction, including increases in serum transaminases (AST and/or ALT), serum bilirubin, and/or alkaline phosphatase, has been infrequently reported with AUGMENTIN or AUGMENTIN ES-600. It has been reported more commonly in the elderly, in males, or in patients on prolonged treatment. The histologic findings on liver biopsy have consisted of cholestatic, hepatocellular, or mixed cholestatic-hepatocellular changes. The onset of signs/symptoms of hepatic dysfunction may occur during or several weeks after therapy has been discontinued. The hepatic dysfunction, which may be severe, is usually reversible. Deaths have been reported [see Contraindications (4.2), Warnings and Precautions (5.4)].

Renal: Interstitial nephritis and hematuria have been reported. Crystalluria has also been reported [see Overdosage (10)].

Hemic and Lymphatic Systems: Anemia, including hemolytic anemia, thrombocytopenia, thrombocytopenic purpura, eosinophilia, leukopenia, and agranulocytosis have been reported during therapy with penicillins. These reactions are usually reversible on discontinuation of therapy and are believed to be hypersensitivity phenomena. There have been reports of increased prothrombin time in patients receiving AUGMENTIN and anticoagulant therapy concomitantly.

Central Nervous System: Agitation, anxiety, behavioral changes, aseptic meningitis, confusion, convulsions, dizziness, insomnia, and reversible hyperactivity have been reported.

Miscellaneous: Tooth discoloration (brown, yellow, or gray staining) has been reported. Most reports occurred in pediatric patients. Discoloration was reduced or eliminated with brushing or dental cleaning in most cases.

7 DRUG INTERACTIONS

7.1 Probenecid

Probenecid decreases the renal tubular secretion of amoxicillin. Concurrent use with AUGMENTIN ES-600 may result in increased and prolonged blood levels of amoxicillin. Co-administration of probenecid is not recommended.

7.2 Oral Anticoagulants

Abnormal prolongation of prothrombin time (increased international normalized ratio [INR]) has been reported in patients receiving amoxicillin and oral anticoagulants. Appropriate monitoring should be undertaken when anticoagulants are prescribed concurrently. Adjustments in the dose of oral anticoagulants may be necessary to maintain the desired level of anticoagulation.

7.3 Allopurinol

The concurrent administration of allopurinol and amoxicillin increases substantially the incidence of rashes in patients receiving both drugs as compared to patients receiving amoxicillin alone. It is not known whether this potentiation of amoxicillin rashes is due to allopurinol or the hyperuricemia present in these patients. There are no data with AUGMENTIN ES-600 and allopurinol administered concurrently.

7.4 Oral Contraceptives

AUGMENTIN ES-600 may affect intestinal flora, leading to lower estrogen reabsorption and reduced efficacy of combined oral estrogen/progesterone contraceptives.

7.5 Effects on Laboratory Tests

High urine concentrations of amoxicillin may result in false-positive reactions when testing for the presence of glucose in urine using CLINITEST®, Benedict's Solution, or Fehling's Solution. Since this effect may also occur with AUGMENTIN ES-600, it is recommended that glucose tests based on enzymatic glucose oxidase reactions be used.

Following administration of amoxicillin to pregnant women, a transient decrease in plasma concentration of total conjugated estriol, estriol-glucuronide, conjugated estrone, and estradiol has been noted.

8 USE IN SPECIFIC POPULATIONS

8.1 Pregnancy

Risk Summary

Available data from published epidemiologic studies and pharmacovigilance case reports over several decades of use with amoxicillin and clavulanate during pregnancy have not established a drug-associated risk of major birth defects, miscarriage, or adverse maternal outcomes. A study in women with preterm prelabor rupture of membranes (PPROM) reported that prophylactic treatment with amoxicillin and clavulanate may be associated with an increased risk of necrotizing enterocolitis in neonates (see Data). Reproduction studies performed in pregnant rodents, given up to approximately 2 times the amount of amoxicillin and 15 times the amount of clavulanate in the Maximum Human Recommended Dose (MHRD) of AUGMENTIN ES-600, revealed no evidence of harm to the fetus (see Data).

The background risk of major birth defects and miscarriage for the indicated populations is unknown. All pregnancies have a background risk of birth defect, loss, or other adverse outcomes. In the U.S. general population, the estimated background risk of major birth defects and miscarriage in clinically recognized pregnancies is 2 to 4% and 15 to 20%, respectively.

Data

Human Data

One randomized, controlled trial included 4,826 pregnant women with premature rupture of fetal membranes who were randomly assigned to 250 mg erythromycin (n=1,197), 250 mg amoxicillin and 125 mg clavulanic acid (amoxicillin and clavulanate, n=1,212), amoxicillin and clavulanate and erythromycin (n=1,192), or placebo (n=1,225) four times daily for 10 days or until delivery. Amoxicillin and clavulanate was associated with a significantly increased rate of proven neonatal necrotizing enterocolitis: 1.9% (n = 24) in the amoxicillin and clavulanate only group versus 0.5% (n = 6) in the placebo group (p = 0.001), and 1.8% (n = 44) in the any amoxicillin and clavulanate group versus 0.7% (n =17) in the no amoxicillin and clavulanate group (p = 0.0005).

Animal Data

Reproduction studies performed in pregnant rats and mice given amoxicillin and clavulanate (2:1 ratio formulation of amoxicillin:clavulanate) at oral doses up to 1200 mg/kg/day revealed no evidence of harm to the fetus due to amoxicillin and clavulanate. The amoxicillin doses in rodents (based on body surface area and assuming a 20 kg child) were approximately 2 times (rats) or equal to (mice) the recommended clinical AUGMENTIN ES-600 dose of 90/6.4 mg/kg/day. For clavulanate, these dose multiples were approximately 15 times and 7.5 times the recommended daily dose of AUGMENTIN ES-600.

8.2 Lactation

Risk Summary

Data from a published clinical lactation study report that amoxicillin is present in human milk. There are reports of diarrhea, irritability, and rash in infants exposed to amoxicillin and clavulanate through breast milk; therefore, infants exposed to AUGMENTIN ES-600 should be monitored for these symptoms. There are no data on the effects of amoxicillin and clavulanate on milk production. The developmental and health benefits of breastfeeding should be considered along with the mother’s clinical need for AUGMENTIN ES-600 and any potential adverse effects on the breastfed child from AUGMENTIN ES-600 or from the underlying maternal condition.

8.4 Pediatric Use

Acute Otitis Media

The safety and effectiveness of AUGMENTIN ES-600 have been established in pediatric patients aged 3 months to 12 years weighing less than or equal to 40 kg, for the treatment of acute otitis media, and the information on this use is discussed throughout the labeling.

The safety and effectiveness of AUGMENTIN ES-600 in pediatric patients younger than 3 months of age have not been established.

The safety and effectiveness of Augmentin ES-600 have not been established in pediatric patients aged 3 months to 12 years weighing more than 40 kg.

Acute Bacterial Sinusitis

The safety and effectiveness of AUGMENTIN ES-600 have been established for the treatment of pediatric patients (3 months to 12 years of age) with acute bacterial sinusitis. This use is supported by evidence from adequate and well-controlled studies of AUGMENTIN XRTM Extended Release Tablets in adults with acute bacterial sinusitis, studies of AUGMENTIN ES-600 in pediatric patients with acute otitis media, and by similar pharmacokinetics of amoxicillin and clavulanate in pediatric patients taking AUGMENTIN ES-600 [see Clinical Pharmacology (12)] and adults taking AUGMENTIN XR.

10 OVERDOSAGE

Following overdosage, patients have experienced primarily gastrointestinal symptoms including stomach and abdominal pain, vomiting, and diarrhea. Rash, hyperactivity, or drowsiness have also been observed in a small number of patients.

In the case of overdosage, discontinue AUGMENTIN ES-600, treat symptomatically, and institute supportive measures as required. If the overdosage is very recent and there is no contraindication, an attempt at emesis or other means of removal of drug from the stomach may be performed. A prospective study of 51 pediatric patients at a poison control center suggested that overdosages of less than 250 mg/kg of amoxicillin are not associated with significant clinical symptoms and do not require gastric emptying.^1

Interstitial nephritis resulting in oliguric renal failure has been reported in a small number of patients after overdosage with amoxicillin.

Crystalluria, in some cases leading to renal failure, has also been reported after amoxicillin overdosage in adult and pediatric patients. In case of overdosage, adequate fluid intake and diuresis should be maintained to reduce the risk of amoxicillin crystalluria.

Renal impairment appears to be reversible with cessation of drug administration. High blood levels may occur more readily in patients with impaired renal function because of decreased renal clearance of both amoxicillin and clavulanate. Both amoxicillin and clavulanate are removed from the circulation by hemodialysis [see Dosage and Administration (2)].

11 DESCRIPTION

AUGMENTIN ES-600 is an oral antibacterial combination consisting of the semisynthetic antibacterial amoxicillin and the beta-lactamase inhibitor, clavulanate potassium (the potassium salt of clavulanic acid). Amoxicillin is an analog of ampicillin, derived from the basic penicillin nucleus, 6-aminopenicillanic acid. The amoxicillin molecular formula is C16 H19 N3 O5 S•3H2 O, and the molecular weight is 419.46. Chemically, amoxicillin is (2 S,5 R,6 R)-6-[(R)-(-)-2-Amino-2-(p-hydroxyphenyl)acetamido]-3,3-dimethyl-7-oxo-4-thia-1-azabicyclo [3.2.0] heptane-2-carboxylic acid trihydrate and may be represented structurally as:

Clavulanic acid is produced by the fermentation of Streptomyces clavuligerus. It is a beta-lactam structurally related to the penicillins and possesses the ability to inactivate a wide variety of beta-lactamases by blocking the active sites of these enzymes. Clavulanic acid is particularly active against the clinically important plasmid-mediated beta-lactamases frequently responsible for transferred drug resistance to penicillins and cephalosporins. The clavulanate potassium molecular formula is C8 H8 KNO5 and the molecular weight is 237.25. Chemically, clavulanate potassium is potassium (Z)-(2R,5R)-3-(2-hydroxyethylidene)-7-oxo-4-oxa-1-azabicyclo[3.2.0]-heptane-2-carboxylate and may be represented structurally as:

Following constitution, each 5 mL of oral suspension contains 600 mg of amoxicillin as the trihydrate and 42.9 mg of clavulanic acid (equivalent to 51.1 mg of clavulanate potassium).

Inactive Ingredients: Aspartame, colloidal silicon dioxide, silicon dioxide, sodium carboxymethylcellulose, strawberry cream flavor, and xanthan gum [see Warnings and Precautions (5.8)]. Each 5 mL of reconstituted AUGMENTIN ES-600 contains approximately 9 mg of potassium and 4 mg of sodium.

12 CLINICAL PHARMACOLOGY

12.1 Mechanism of Action

AUGMENTIN ES-600 is an antibacterial drug [see Microbiology (12.4)].

12.3 Pharmacokinetics

The pharmacokinetics of amoxicillin and clavulanate were determined in a study of 19 pediatric patients, 8 months to 11 years, given AUGMENTIN ES-600 at an amoxicillin dose of 45 mg/kg q12h with a snack or meal. The mean plasma amoxicillin and clavulanate pharmacokinetic parameter values are listed in the Table 3.

Table 3. Mean (±SD) Plasma Amoxicillin and Clavulanate Pharmacokinetic Parameter Values Following Administration of 45 mg/kg of AUGMENTIN ES-600 Every 12 Hours to Pediatric Patients

PARAMETER | AMOXICILLIN | CLAVULANATE
Cmax (mcg/mL) | 15.7 ± 7.7 | 1.7 ± 0.9
Tmax (hr) | 2.0 (1.0 to 4.0) | 1.1 (1.0 to 4.0)
AUC0-T (mcg*hr/mL) | 59.8 ± 20.0 | 4.0 ± 1.9
T½ (hr) | 1.4 ± 0.3 | 1.1 ± 0.3
CL/F (L/hr/kg) | 0.9 ± 0.4 | 1.1 ± 1.1
* Arithmetic mean ± standard deviation, except Tmax values which are medians (ranges).

The effect of food on the oral absorption of AUGMENTIN ES-600 has not been studied.

Approximately 50% to 70% of the amoxicillin and approximately 25% to 40% of the clavulanic acid are excreted unchanged in urine during the first 6 hours after administration of 10 mL of 250 mg/5 mL suspension of AUGMENTIN.

Neither component in AUGMENTIN ES-600 is highly protein-bound; clavulanic acid has been found to be approximately 25% bound to human serum and amoxicillin approximately 18% bound.

Oral administration of a single dose of AUGMENTIN ES-600 at 45 mg/kg (based on the amoxicillin component) to pediatric patients, 9 months to 8 years, yielded the following pharmacokinetic data for amoxicillin in plasma and middle ear fluid (MEF):

Table 4. Amoxicillin Concentrations in Plasma and Middle Ear Fluid Following Administration of 45 mg/kg of AUGMENTIN ES-600 to Pediatric Patients*
Timepoint |  | Amoxicillin concentration in plasma (mcg/mL) | Amoxicillin concentration in MEF (mcg/mL)
1 hour | mean median range | 7.7 9.3 1.5 to 14.0 (n = 5) | 3.2 3.5 0.2 to 5.5 (n = 4)
2 hour | mean median range | 15.7 13.0 11.0 to 25.0 (n = 7) | 3.3 2.4 1.9 to 6 (n = 5)
3 hour | mean median range | 13.0 12.0 5.5 to 21.0 (n = 5) | 5.8 6.5 3.9 to 7.4 (n = 5)
* Dose administered immediately prior to eating.

Amoxicillin diffuses readily into most body tissues and fluids, with the exception of the brain and spinal fluid. The results of experiments involving the administration of clavulanic acid to animals suggest that this compound, like amoxicillin, is well distributed in body tissues.

Drug Interaction Studies
Clinical Studies
Concurrent administration of probenecid delays amoxicillin excretion but does not delay renal excretion of clavulanic acid.

12.4 Microbiology

Mechanism of Action

Amoxicillin is a semisynthetic antibacterial with a broad spectrum of bactericidal activity against many gram-positive and gram-negativemicroorganisms. Amoxicillin is, however, susceptible to degradation by beta-lactamases, and therefore, its spectrum of activity does not include organisms which produce these enzymes. Clavulanic acid is a beta-lactam, structurally related to penicillin, which possesses the ability to inactivate a wide range of beta-lactamase enzymes commonly found in microorganisms resistant to penicillins and cephalosporins. In particular, it has good activity against the clinically important plasmid-mediated beta-lactamases frequently found responsible for transferred drug resistance.

The clavulanic acid component of AUGMENTIN ES-600 protects amoxicillin from degradation by beta-lactamase enzymes and effectively extends the antibacterial spectrum of amoxicillin to include many bacteria normally resistant to amoxicillin and other beta-lactam antibacterials. Thus, AUGMENTIN ES-600 possesses the distinctive properties of a broad spectrum antibacterial and a beta-lactamase inhibitor.

Antimicrobial Activity

Amoxicillin/clavulanic acid has been shown to be active against most isolates of the following microorganisms, both in vitro and in clinical infections [see Indications and Usage (1)].

Gram-Positive bacteria:

Streptococcus pneumoniae (including isolates with penicillin MICs less than or equal to 2 mcg/mL)

Gram-Negative bacteria:

Haemophilus influenzae (including beta-lactamase-producing isolates)

Moraxella catarrhalis (including beta-lactamase-producing isolates)

The following in vitro data are available, but their clinical significance is unknown. At least 90% of the following microorganisms exhibit in vitro minimum inhibitory concentrations (MICs) less than or equal to the susceptible breakpoint for amoxicillin/clavulanic acid. However, the safety and efficacy of amoxicillin/clavulanic acid in treating infections due to these microorganisms have not been established in adequate and well-controlled trials.

Gram-Positive bacteria:

Staphylococcus aureus (including beta-lactamase-producing isolates)

Staphylococci which are resistant to methicillin/oxacillin must be considered resistant to amoxicillin/clavulanic acid.

Streptococcus pyogenes

S. pyogenes do not produce beta-lactamase, and therefore, are susceptible to amoxicillin alone. Adequate and well-controlled clinical trials have established the effectiveness of amoxicillin alone in treating certain clinical infections due to S. pyogenes.

Susceptibility Test Methods:

For specific information regarding susceptibility test interpretive criteria and associated test methods and quality control standards recognized by FDA for this drug, please see: https://www.fda.gov/STIC.

13 NONCLINICAL TOXICOLOGY

13.1 Carcinogenesis, Mutagenesis, Impairment of Fertility

Long-term studies in animals have not been performed to evaluate carcinogenic potential.

Amoxicillin and clavulanate (4:1 ratio formulation of amoxicillin:clavulanate) was non-mutagenic in the Ames bacterial mutation assay, and the yeast gene conversion assay. Amoxicillin and clavulanate was weakly positive in the mouse lymphoma assay, but the trend toward increased mutation frequencies in this assay occurred at concentrations that were also associated with decreased cell survival. Amoxicillin and clavulanate was negative in the mouse micronucleus test, and in the dominant lethal assay in mice. Clavulanate potassium alone was tested in the Ames bacterial mutation assay and in the mouse micronucleus test and was negative in each of these assays.

Amoxicillin and clavulanate (2:1 ratio formulation of amoxicillin:clavulanate) at oral doses of up to 1,200 mg/kg/day was found to have no effect on fertility and reproductive performance in rats. Based on body surface area (assuming a 20 kg child), this dose of amoxicillin is approximately 2 times the recommended clinical AUGMENTIN ES-600 dose of 90/6.4 mg/kg/day. For clavulanate, the dose multiple is approximately 15 times higher than the recommended clinical daily dose, also based on body surface area.

14 CLINICAL STUDIES

Two clinical studies were conducted in pediatric patients with acute otitis media. A non-comparative, open-label study assessed the bacteriologic and clinical efficacy of AUGMENTIN ES-600 (90/6.4 mg/kg/day, divided every 12 hours) for 10 days in 521 pediatric patients (3 to 50 months) with acute otitis media. The primary objective was to assess bacteriological response in children with acute otitis media due to S. pneumoniae with amoxicillin/clavulanic acid MICs of 4 mcg/mL. The study sought the enrollment of patients with the following risk factors: Failure of antibacterial therapy for acute otitis media in the previous 3 months, history of recurrent episodes of acute otitis media, 2 years or younger, or daycare attendance. Prior to receiving AUGMENTIN ES-600, all patients had tympanocentesis to obtain middle ear fluid for bacteriological evaluation. Patients from whom S. pneumoniae (alone or in combination with other bacteria) was isolated had a second tympanocentesis 4 to 6 days after the start of therapy. Clinical assessments were planned for all patients during treatment (4 to 6 days after starting therapy), as well as 2 to 4 days post-treatment and 15 to 18 days post-treatment. Bacteriological success was defined as the absence of the pretreatment pathogen from the on-therapy tympanocentesis specimen. Clinical success was defined as improvement or resolution of signs and symptoms. Clinical failure was defined as lack of improvement or worsening of signs and/or symptoms at any time following at least 72 hours of AUGMENTIN ES-600; patients who received an additional systemic antibacterial drug for otitis media after 3 days of therapy were considered clinical failures. Bacteriological eradication on therapy (day 4 to 6 visit) in the per protocol population is summarized in Table 5.

Table 5. Bacteriologic Eradication Rates in the Per Protocol Population

 | Bacteriologic Eradication on Therapy
Pathogen | n/N | % | 95% CI*
All S. pneumoniae | 121/123 | 98 | (94.3, 99.8)
S. pneumoniae with penicillin MIC equal to 2 mcg/mL | 19/19 | 100 | (82.4, 100.0)
S. pneumoniae with penicillin MIC equal to 4 mcg/mL | 12/14 | 86 | (57.2, 98.2)
H. influenzae | 75/81 | 93 | (84.6, 97.2)
M. catarrhalis | 11/11 | 100 | (71.5, 100.0)
* CI equals confidence intervals; 95% CIs are not adjusted for multiple comparisons.

Clinical assessments were made in the per protocol population 2 to 4 days post-therapy and 15 to 18 days post-therapy. Patients who responded to therapy 2 to 4 days post-therapy were followed for 15 to 18 days post-therapy to assess them for acute otitis media. Non-responders at 2 to 4 days post-therapy were considered failures at the latter timepoint. The clinical assessments in the per protocol population are presented in Table 6.

Table 6. Clinical Assessments in the Per Protocol Population (Includes S. pneumoniae Patients with Penicillin MICs equal to 2 or 4 mcg/mL*)
 | 2 to 4 Days Post-Therapy (Primary Endpoint)
Pathogen | n/N | % | 95% CI†
All S. pneumoniae | 122/137 | 89 | (82.6, 93.7)
S. pneumoniae with penicillin MIC equal to 2 mcg/mL | 17/20 | 85 | (62.1, 96.8)
S. pneumoniae with penicillin MIC equal to 4 mcg/mL | 11/14 | 79 | (49.2, 95.3)
H. influenzae | 141/162 | 87 | (80.9, 91.8)
M. catarrhalis | 22/26 | 85 | (65.1, 95.6)

 | 15 to 18 Days Post-Therapy‡ (Secondary Endpoint)
Pathogen | n/N | % | 95% CI†
All S. pneumoniae | 95/136 | 70 | (61.4, 77.4)
S. pneumoniae with penicillin MIC equal to 2 mcg/mL | 11/20 | 55 | (31.5, 76.9)
S. pneumoniae with penicillin MIC equal to 4 mcg/mL | 5/14 | 36 | (12.8, 64.9)
H. influenzae | 106/156 | 68 | (60.0, 75.2)
M. catarrhalis | 14/25 | 56 | (34.9, 75.6)
* S. pneumoniae strains with penicillin MICs of 2 or 4 mcg/mL are considered resistant to penicillin.
† CI equals confidence intervals; 95% CIs are not adjusted for multiple comparisons.
‡ Clinical assessments at 15 to 18 days post-therapy may have been confounded by viral infections and new episodes of acute otitis media with time elapsed post-treatment.

In the intent-to-treat analysis, overall clinical outcomes at 2 to 4 days and 15 to 18 days post-treatment in patients with S. pneumoniae with penicillin MIC equal to 2 mcg/mL and 4 mcg/mL were 29/41 (71%) and 17/41 (42%), respectively.

15 REFERENCES

1. Swanson-Biearman B, Dean BS, Lopez G, Krenzelok EP. The effects of penicillin and cephalosporin ingestions in children less than six years of age. Vet Hum Toxicol. 1988; 30:66-67.

16 HOW SUPPLIED/STORAGE AND HANDLING

How Supplied

AUGMENTIN ES-600 (amoxicillin and clavulanate potassium) for oral suspension is a strawberry cream-flavored powder for oral suspension. Following constitution, each 5 mL of oral suspension contains 600 mg of amoxicillin as the trihydrate and 42.9 mg of clavulanic acid as the potassium salt. Strawberry cream-flavored powder for oral suspension. Following constitution, each 5 mL of oral suspension contains 600 mg of amoxicillin as the trihydrate and 42.9 mg of clavulanic acid as the potassium salt (equivalent to 51.1 mg of clavulanate potassium).

AUGMENTIN ES-600 is supplied as follows:
• NDC 81964-003-51 75 mL bottle
• NDC 81964-003-69 125 mL bottle
• NDC 81964-003-54 200 mL bottle

Storage

Store dry powder for oral suspension at or below 25°C (77°F). Dispense in original container. Store reconstituted suspension under refrigeration. Discard unused suspension after 10 days.

17 PATIENT COUNSELING INFORMATION

Administration Instructions

Inform patients to take AUGMENTIN ES-600 every 12 hours with a meal or snack to reduce the possibility of gastrointestinal upset. If diarrhea develops and is severe or lasts more than 2 or 3 days, they should call their doctor [see Dosage and Administration (2.1), Warnings and Precautions (5.5)].

Allergic Reactions

Counsel patients that AUGMENTIN ES-600 contains a penicillin class drug product that can cause allergic reactions in some individuals [see Warnings and Precautions (5.1, 5.3)].

Severe Cutaneous Adverse Reactions (SCAR)

Advise patients about the signs and symptoms of serious skin manifestations. Instruct patients to stop taking AUGMENTIN ES-600 immediately and promptly report the first signs or symptoms of skin rash, mucosal lesions, or any other sign of hypersensitivity [see Warnings and Precautions (5.2)].

Diarrhea

Counsel patients that diarrhea is a common problem caused by antibacterial drugs, including AUGMENTIN ES-600, which usually ends when the antibacterial is discontinued. Sometimes after starting treatment with antibacterial drugs, patients can develop watery and bloody stools (with or without stomach cramps and fever) even as late as 2 or more months after having taken the last dose of the antibacterial drug. If this occurs, patients should contact their physician as soon as possible [see Warnings and Precautions (5.5)].

Phenylketonuria

Counsel patients with phenylketonuria: Each 5 mL of suspension of AUGMENTIN ES-600 contains 7 mg phenylalanine. [see Warnings and Precautions (5.8)].

Antibacterial Resistance

Patients should be counseled that antibacterial drugs, including AUGMENTIN ES-600, should only be used to treat bacterial infections. Antibacterial drugs do not treat viral infections (e.g., the common cold). When AUGMENTIN ES-600 is prescribed to treat a bacterial infection, patients should be told that although it is common to feel better early in the course of therapy, the medication should be taken exactly as directed. Skipping doses or not completing the full course of therapy may: (1) decrease the effectiveness of the immediate treatment, and (2) increase the likelihood that bacteria will develop resistance and will not be treatable by AUGMENTIN ES-600 or other antibacterial drugs in the future [see Warnings and Precautions (5.9)].

Storage Instructions

Keep suspension refrigerated. Shake well before using. When dosing a child with the suspension (liquid) of AUGMENTIN ES-600, use a dosing spoon or medicine dropper. Be sure to rinse the spoon or dropper after each use. Bottles of suspension of AUGMENTIN ES-600 may contain more liquid than required. Follow your doctor's instructions about the amount to use and the days of treatment your child requires. Discard any unused medicine.

Manufactured by:

USAntibiotics, LLC
Bristol, TN 37620 (USA)

AUGMENTIN ES-600 and AUGMENTIN XR are registered trademarks of GlaxoSmithKline and are licensed to USAntibiotics, LLC.

CLINITEST is a registered trademark of Miles, Inc.

FLAVORx is a trademark of FLAVORx. Inc.

PRINICPLE DISPLAY PANEL: Container Label - 75 mL

NDC 81964-003-51
600 mg/42.9 mg per 5 mL

AUGMENTIN ES-600®
amoxicillin and
clavulanate potassium
for oral suspension, USP

When reconstituted, each 5 mL contains:
AMOXICILLIN, 600 mg
as the trihydrate, and
CLAVULANIC ACID, 42.9 mg
(equivalent to 51.1 mg of clavulanate potassium)

75 mL (when reconstituted)

USANTIBIOTICS Rx only

PRINICPLE DISPLAY PANEL: Container Label - 125 mL

NDC 81964-003-69
600 mg/42.9 mg per 5 mL

AUGMENTIN ES-600®
amoxicillin and
clavulanate potassium
for oral suspension, USP

When reconstituted, each 5 mL contains:
AMOXICILLIN, 600 mg
as the trihydrate, and
CLAVULANIC ACID, 42.9 mg
(equivalent to 51.1 mg of clavulanate potassium)

125 mL (when reconstituted)

USANTIBIOTICS Rx only

PRINICPLE DISPLAY PANEL: Container Label - 200 mL

NDC 81964-003-54

600 mg/42.9 mg per 5 mL

AUGMENTIN ES-600®
amoxicillin and
clavulanate potassium
for oral suspension, USP

When reconstituted, each 5 mL contains:
AMOXICILLIN, 600 mg
as the trihydrate, and
CLAVULANIC ACID, 42.9 mg
(equivalent to 51.1 mg of clavulanate potassium)

200 mL (when reconstituted)

USANTIBIOTICS Rx only